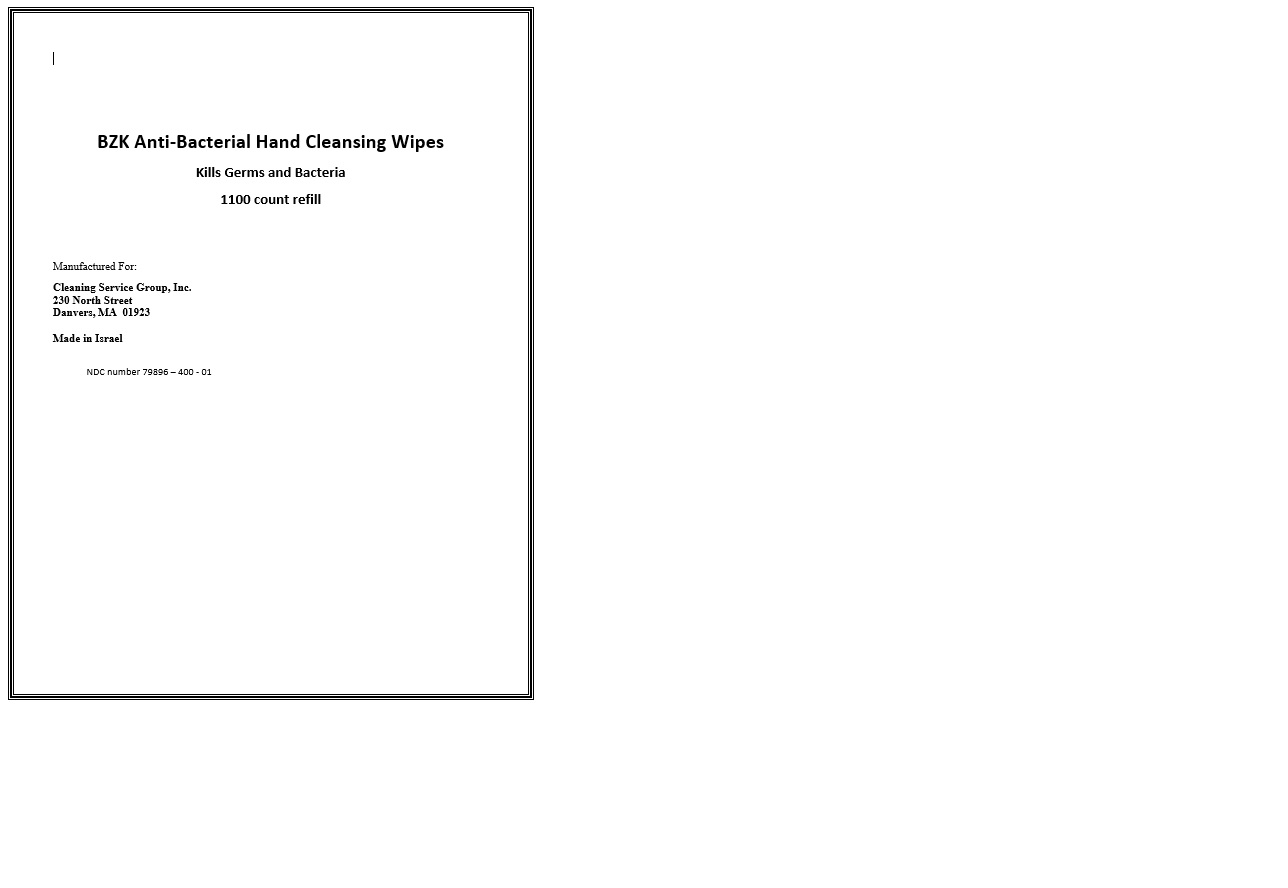 DRUG LABEL: BZK Anti-Bacterial Hand Cleansing Wipes
NDC: 79896-400 | Form: CLOTH
Manufacturer: Cleaning Service Group, Inc.
Category: otc | Type: HUMAN OTC DRUG LABEL
Date: 20200728

ACTIVE INGREDIENTS: BENZALKONIUM CHLORIDE 0.001 1/1 1
INACTIVE INGREDIENTS: CHAMOMILE; ALLANTOIN; ANHYDROUS CITRIC ACID; PANTHENOL; POTASSIUM SORBATE; PEG-12 DIMETHICONE (300 CST); ALPHA-TOCOPHEROL ACETATE; WATER; BENZYL ALCOHOL; GLYCERIN; EDETATE SODIUM; SODIUM BENZOATE; ALOE VERA LEAF; DECYL GLUCOSIDE; SODIUM HYDROXYMETHYLGLYCINATE

BZK Anti-Bacterial Hand Cleansing Wipes

Active ingredient

Benzalkonium chloride

Purpose

Antibacterial

Directions

Sanitize hands or other affected area. Discard in trash after use.

Inactive ingredients

Benzyl alcohol, Peg-12 Dimethicone, alpha-tocopherol acetate, decyl glucoside, glycerin, edetate sodium, potassium sorbate, sodium benzoate, sodium hydroxymethylglycinate, chamomile, allantoin, aloe vera leaf, anhydrous citric acid, pathenol, water

Warnings

For external use only.

Keep out of eyes. In case of eye contact, rinse with water. If irritation develops, discontinue use. Consult doctor if irritation persists for more than 72 hours.

If swallowed, seek medical attention or contact a Poison Control Center.

Keep out of the reach of children.

Keep out of reach of children, except with adult supervision.

To use

Locate tear-notch on top of refill pouch. Tear straight across to open. Pull first wipe from center of roll through the pouch center opening. Thread wipe through dispenser nozzle. Use only upward pull dispensers.